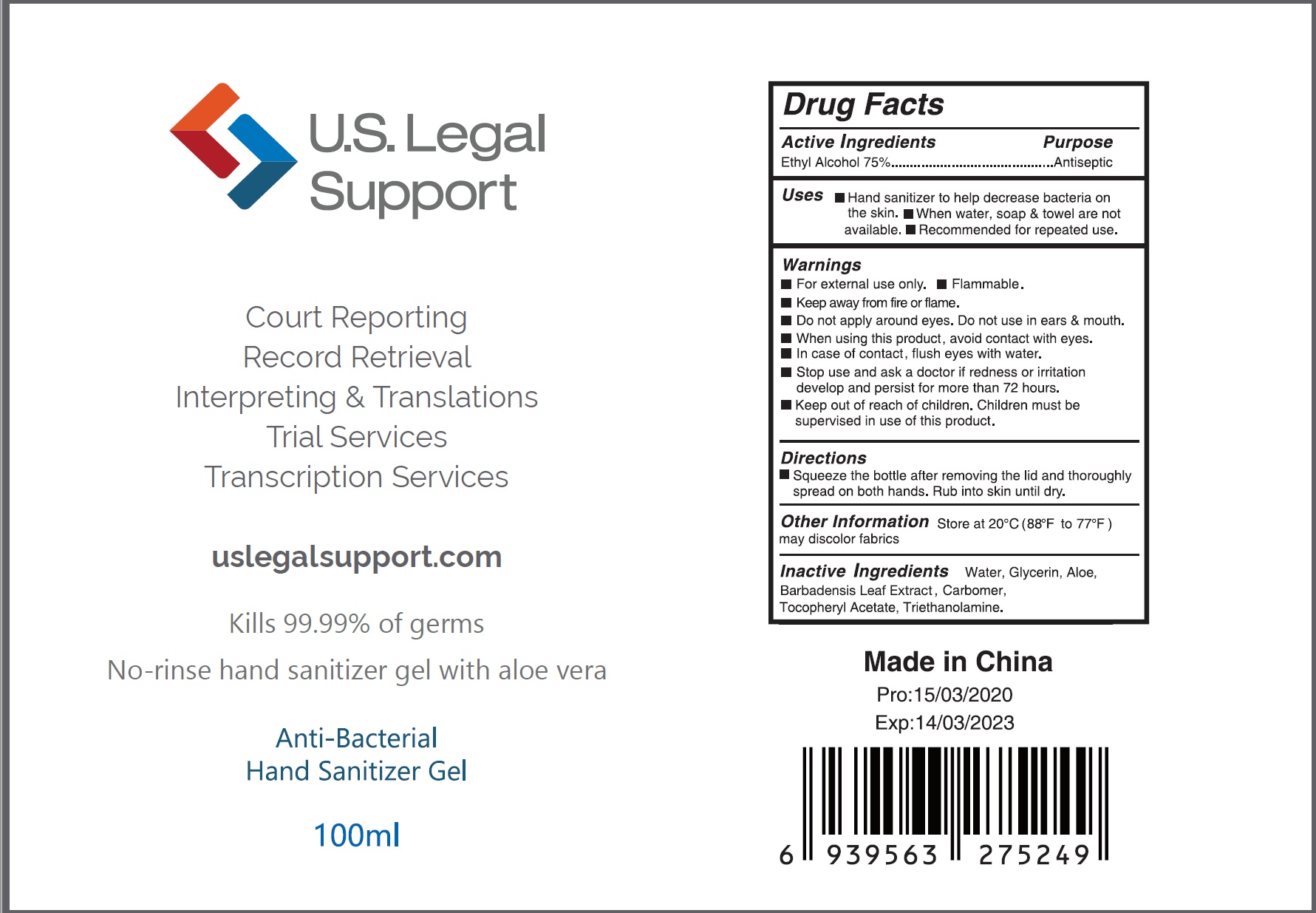 DRUG LABEL: U.S. Legal Support Hand Sanitizer
NDC: 73788-107 | Form: GEL
Manufacturer: Hangzhou Huiji Biotechnology Co., Ltd.
Category: otc | Type: HUMAN OTC DRUG LABEL
Date: 20220224

ACTIVE INGREDIENTS: ALCOHOL 75 mL/100 mL
INACTIVE INGREDIENTS: ALPHA-TOCOPHEROL ACETATE; TROLAMINE; CARBOMER 934; WATER; GLYCERIN; ALOE VERA LEAF

73788-107 75% alcohol U.S. Legal Support Anti-Bacterial Hand Sanitizer Gel

Active Ingredient

Ethyl Alcohol 75%

Purpose

Antiseptic

Use

UsesI I Hand sanitizer to help decrease bacteria on
the skin. When water, soap & towel are not
available. Recommended for repeated use.

WARNINGS

For external use only. Flammable.
Keep away from fire or flame.
Do not apply around eyes. Do not use in ears & mouth.
When using this product, avoid contact with eyes.
In case of contact, flush eyes with water.
Stop use and ask a doctor if redness or irritation
develop and persist for more than 72 hours.
Keep out of reach of children. Children must be
supervised in use of this product.

Keep out of reach of children. Children must be
supervised in use of this product.

Directions

Squeeze the bottle after removing the lid and thoroughly
spread on both hands. Rub into skin until dry.

Other Information

1 Do not store above 105°F
1 May discolor some fabrics

Inactive ingredients

Inactive Ingredients Water, Glycerin, Aloe
Barbadensis Leaf Extract, Carbomer,
Tocophery| Acetate, Triethanolamine.